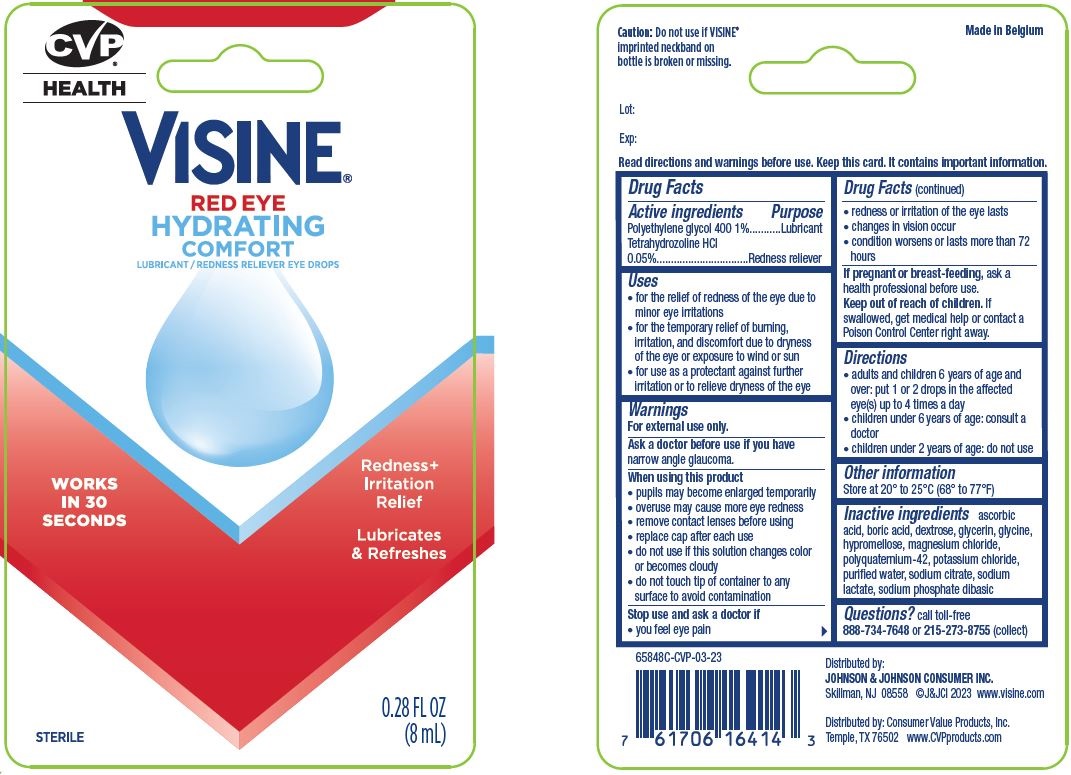 DRUG LABEL: Visine Red Eye Hydrating Comfort, CVP
NDC: 66715-6584 | Form: SOLUTION/ DROPS
Manufacturer: Lil' Drug Store Products, Inc.
Category: otc | Type: HUMAN OTC DRUG LABEL
Date: 20240119

ACTIVE INGREDIENTS: TETRAHYDROZOLINE HYDROCHLORIDE 0.5 mg/1 mL; POLYETHYLENE GLYCOL 400 10 mg/1 mL
INACTIVE INGREDIENTS: BORIC ACID; HYPROMELLOSE, UNSPECIFIED; SODIUM CITRATE, UNSPECIFIED FORM; POTASSIUM CHLORIDE; WATER; SODIUM PHOSPHATE, DIBASIC, ANHYDROUS; ASCORBIC ACID; MAGNESIUM CHLORIDE; SODIUM LACTATE; POLIXETONIUM CHLORIDE; DEXTROSE, UNSPECIFIED FORM; GLYCERIN; GLYCINE

Visine® Red Eye Hydrating Comfort, CVP® HEALTH

Active ingredients

Polyethylene glycol 400 1%

Tetrahydrozoline HCl 0.05%

Purpose

Lubricant

Redness reliever

Uses

- for the relief of redness of the eye due to minor eye irritations
- for the temporary relief of burning, irritation, and discomfort due to dryness of the eye or exposure to wind or sun
- for use as a protectant against further irritation or to relieve dryness of the eye

Warnings

For external use only.

Ask a doctor before use if you have narrow angle glaucoma.

When using this product

- pupils may become enlarged temporarily
- overuse may cause more eye redness
- remove contact lenses before using
- replace cap after each use
- do not use if this solution changes color or becomes cloudy
- do not touch tip of container to any surface to avoid contamination

Stop use and ask a doctor if

- you feel eye pain
- redness or irritation of the eye lasts
- changes in vision occur
- condition worsens or lasts more than 72 hours

If pregnant or breast-feeding, ask a health professional before use.

Keep out of reach of children. If swallowed, get medical help or contact a Poison Control Center right away.

Directions

- adults and children 6 years of age and over: put 1 or 2 drops in the affected eye(s) up to 4 times a day
- children under 6 years of age: consult a doctor
- children under 2 years of age: do not use

Other information

Store at 20° to 25°C (68° to 77°F)

Inactive ingredients

ascorbic acid, boric acid, dextrose, glycerin, glycine, hypromellose, magnesium chloride, polyquaternium-42, potassium chloride, purified water, sodium citrate, sodium lactate, sodium phosphate dibasic

Questions?

Questions? call toll-free
888-734-7648 or 215-273-8755 (collect)

Visine® Red Eye Hydrating Comfort, CVP® Health

[CVP® Health logo]

VISINE®

RED EYE

HYDRATING

COMFORT

LUBRICAN/REDNESS RELIEVER EYE DROPS

WORKS

IN 30

SECONDS

Redness +

Irritation

Relief

Lubricates

& Refreshes

STERILE

0.8 FL OZ

(8mL)